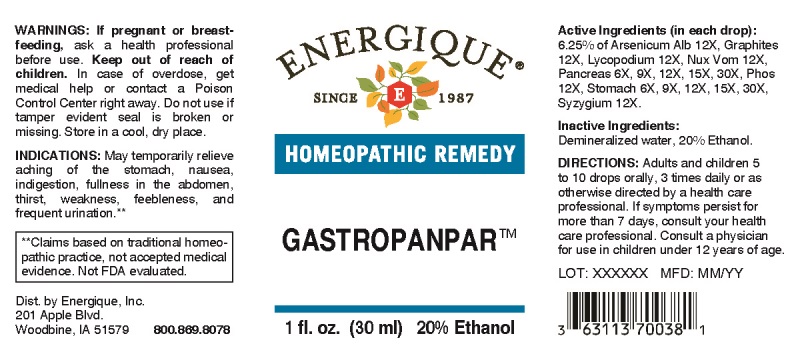 DRUG LABEL: Gastropanpar
NDC: 44911-0073 | Form: LIQUID
Manufacturer: Energique, Inc.
Category: homeopathic | Type: HUMAN OTC DRUG LABEL
Date: 20241024

ACTIVE INGREDIENTS: SUS SCROFA PANCREAS 6 [hp_X]/1 mL; SUS SCROFA STOMACH 6 [hp_X]/1 mL; ARSENIC TRIOXIDE 12 [hp_X]/1 mL; GRAPHITE 12 [hp_X]/1 mL; LYCOPODIUM CLAVATUM SPORE 12 [hp_X]/1 mL; STRYCHNOS NUX-VOMICA SEED 12 [hp_X]/1 mL; PHOSPHORUS 12 [hp_X]/1 mL; SYZYGIUM CUMINI SEED 12 [hp_X]/1 mL
INACTIVE INGREDIENTS: WATER; ALCOHOL

DRUG FACTS:

ACTIVE INGREDIENTS:

(in each drop): 6.25% of Arsenicum Album 12X, Graphites 12X, Lycopodium Clavatum 12X, Nux Vomica 12X, Pancreas Suis 6X, 9X, 12X, 15X, 30X, Phosphorus 12X, Stomach (Suis) 6X, 9X, 12X, 15X, 30X, Syzygium Jambolanum 12X.

INDICATIONS:

May temporarily relieve aching of the stomach, nausea, indigestion, fullness in the abdomen, thirst, weakness, feebleness, and frequent urination.

**Claims based on traditional homeopathic practice, not accepted medical evidence. Not FDA evaluated.

WARNINGS:

If pregnant or breast-feeding, ask a health professional before use.

Keep out of reach of children. In case of overdose, get medical help or contact a Poison Control Center right away.

Do not use if tamper evident seal is broken or missing. Store in a cool, dry place.

DIRECTIONS:

Adults and children 5 to 10 drops orally, 3 times daily or as otherwise directed by a health care professional. If symptoms persist for more than 7 days, consult your health care professional. Consult a physician for use in children under 12 years of age.

INACTIVE INGREDIENTS:

Demineralized water, 20% Ethanol.

Keep out of reach of children. In case of overdose, get medical help or contact a Poison Control Center right away.

INDICATIONS:

May temporarily relieve aching of the stomach, nausea, indigestion, fullness in the abdomen, thirst, weakness, feebleness, and frequent urination.

**Claims based on traditional homeopathic practice, not accepted medical evidence. Not FDA evaluated.

QUESTIONS:

Dist. by Energique, Inc.

201 Apple Blvd

Woodbine, IA 51579 800.869.8078

PACKAGE LABEL DISPLAY:

ENERGIQUE

since 1987

HOMEOPATHIC REMEMDY

GASTROPANPAR

1 fl. oz. (30 ml)